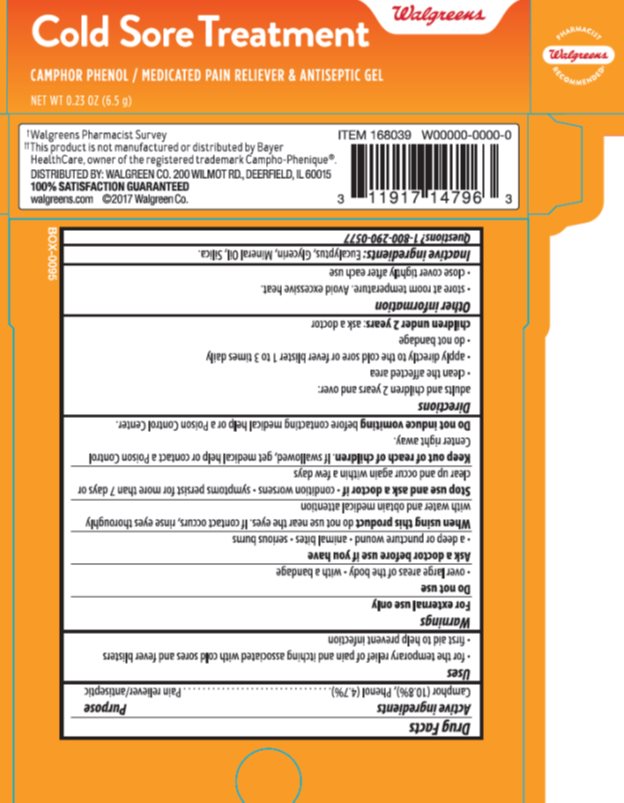 DRUG LABEL: Walgreens Camphor Phenol Gel
NDC: 0363-9425 | Form: GEL
Manufacturer: Walgreens
Category: otc | Type: HUMAN OTC DRUG LABEL
Date: 20170831

ACTIVE INGREDIENTS: CAMPHOR (SYNTHETIC) 10.8 mg/1 g; PHENOL 4.7 mg/1 g
INACTIVE INGREDIENTS: LIGHT MINERAL OIL 77.75 mg/1 g; SILICON DIOXIDE 5.75 mg/1 g; GLYCERIN 0.5 mg/1 g; EUCALYPTUS OIL 0.500 mg/1 g

Drug Facts

Active ingredient

Camphor (10.8%), Phenol (4.7%)

Purpose

Pain reliever/antiseptic

Keep Out of Reach of Children

If swallowed, get medical help or contact a Poison Control Center right away. Do not induce vomiting before contacting medical help or a Poison Control Center.

Uses

For the temporary relief of pain and itching associated with cold sores and fever blisters. First aid to help prevent infection.

Warnings

For external use only. Do not use over large areas of the body or with a bandage. Ask a doctor before use if you have a deep or puncture wound. Animal bites. Serious burns. When using this product do not use near the eye. If contact occurs, rinse eyes thoroughly with water and obtain medical attention.

Directions

Adults and children 2 years or over: clean the affected area. Apply directly to the cold sore or fever blister 1 to 3 times daily. Do not bandage. Children under 2 years: ask a doctor.

Inactive Ingredients

Eucalyptus, Glycerin, Mineral Oil, Silica.